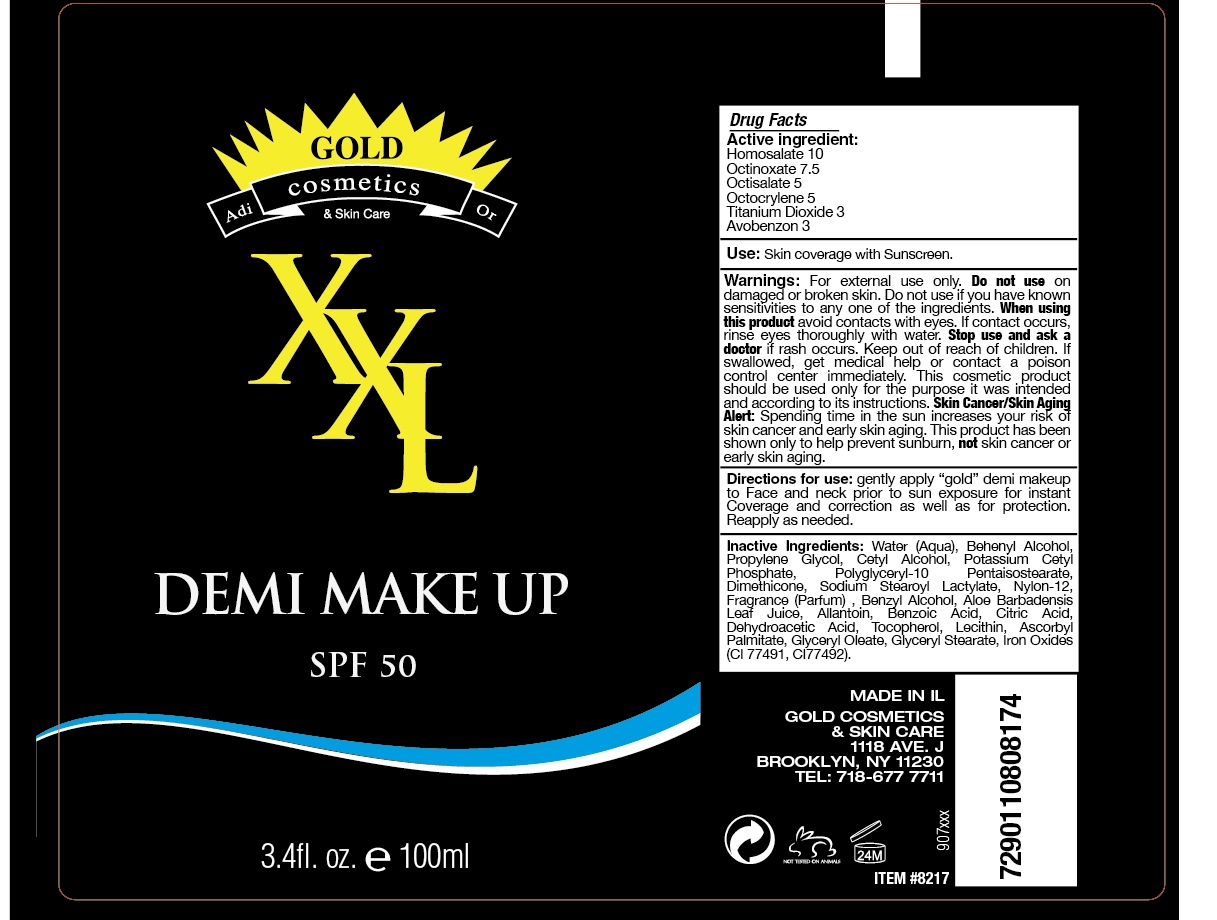 DRUG LABEL: XXL Demi Make Up SPF 50
NDC: 69435-1803 | Form: CREAM
Manufacturer: Peer Pharma Ltd.
Category: otc | Type: HUMAN OTC DRUG LABEL
Date: 20180524

ACTIVE INGREDIENTS: OCTOCRYLENE 5 g/100 mL; OCTISALATE 5 g/100 mL; AVOBENZONE 3 g/100 mL; HOMOSALATE 2 g/100 mL; OCTINOXATE 7 g/100 mL; TITANIUM DIOXIDE 3 g/100 mL
INACTIVE INGREDIENTS: PHENOXYETHANOL; BENZOIC ACID; NYLON-12; ALLANTOIN; DOCOSANOL; DEHYDROACETIC ACID; ASCORBYL PALMITATE; GLYCERYL MONOSTEARATE; CETOSTEARYL ALCOHOL; CETEARYL GLUCOSIDE; GLYCERYL OLEATE; BENZYL ALCOHOL; POTASSIUM CETYL PHOSPHATE; FERRIC OXIDE RED; DIMETHICONE; PROPYLENE GLYCOL; ALOE VERA LEAF; EGG PHOSPHOLIPIDS; CITRIC ACID MONOHYDRATE; POLYGLYCERIN-10; TOCOPHEROL; SODIUM STEAROYL LACTYLATE; WATER

Gold Cosmetics XXL Demi Make Up SPF 50

PACKAGE LABEL

ACTIVE INGREDIENT

Octinoxate 7%

Octocrylene 5%

Octisalate 5%

Avobenzone 3%

Homosalate 2%

Titanium Dioxide 3%

Keep out of reach of children.

PURPOSE

Provides SPF 50 protection

INDICATIONS AND USAGE

Directions for use: gently apply "gold" demi makeup to face and neck prior to sun exposure for instant coverage and correction as well as for protection. Reapply as needed.

DOSAGE AND ADMINISTRATION

Directions for use: gently apply "gold" demi makeup to face and neck prior to sun exposure for instant coverage and correction as well as for protection. Reapply as needed.